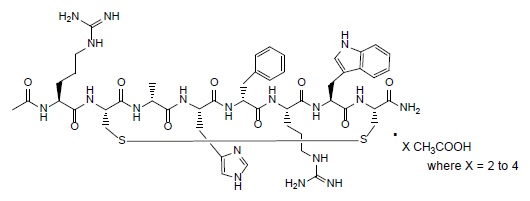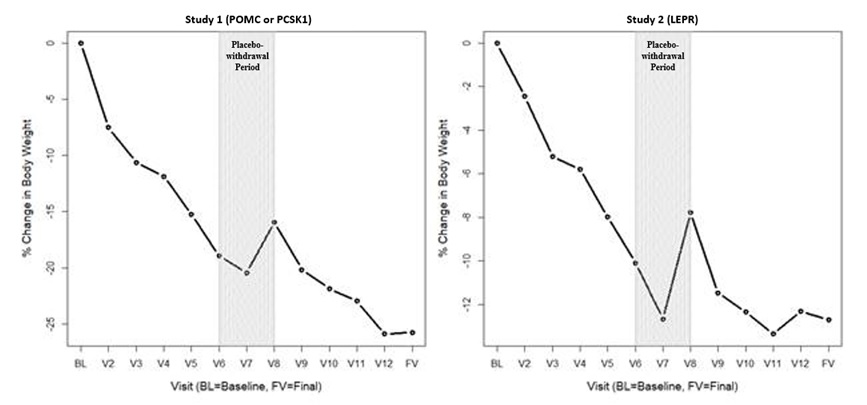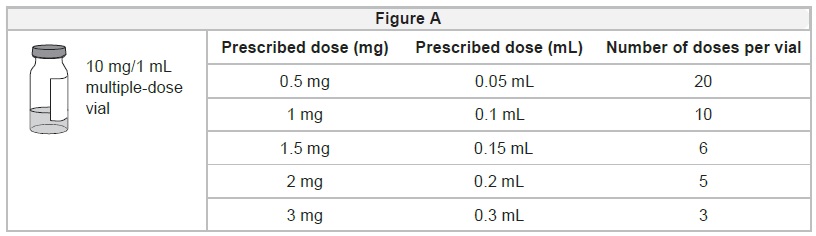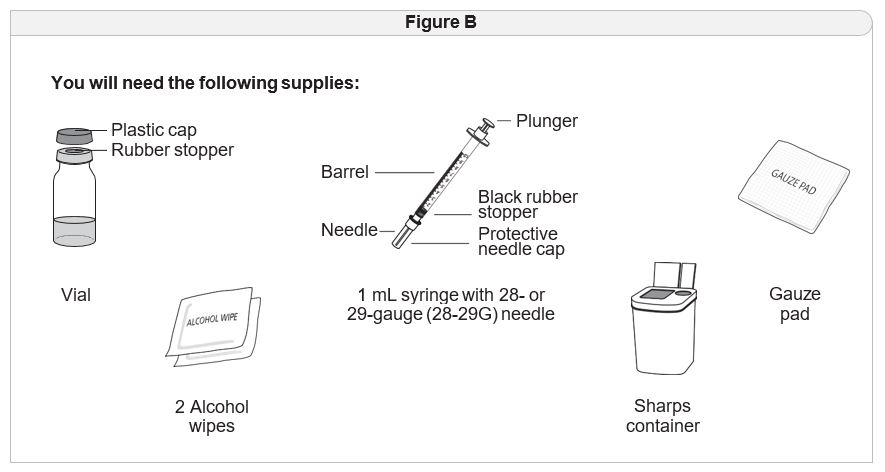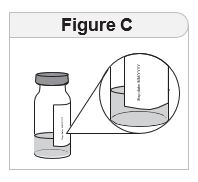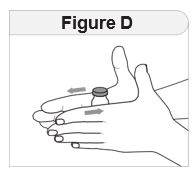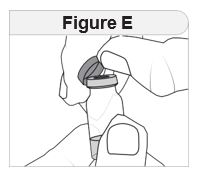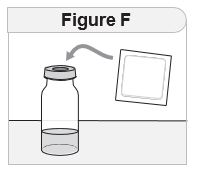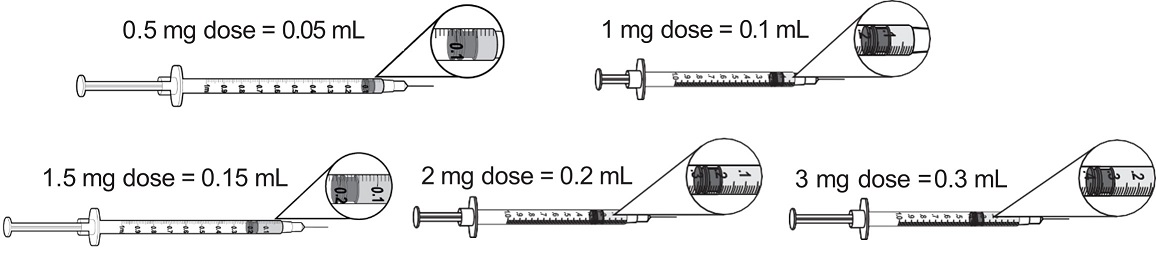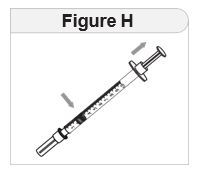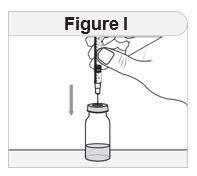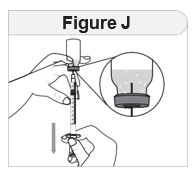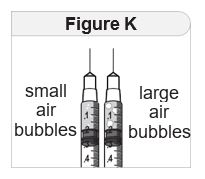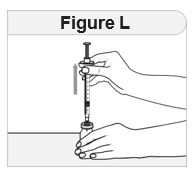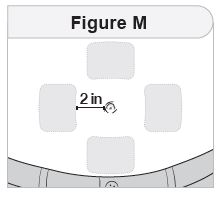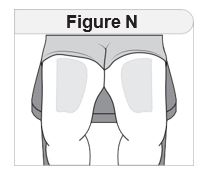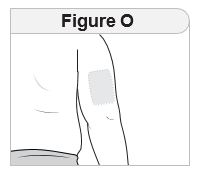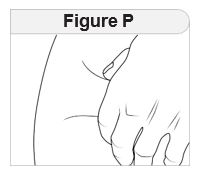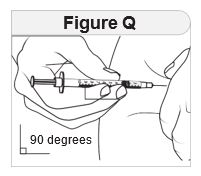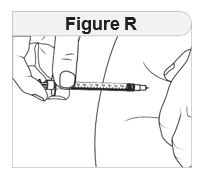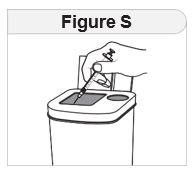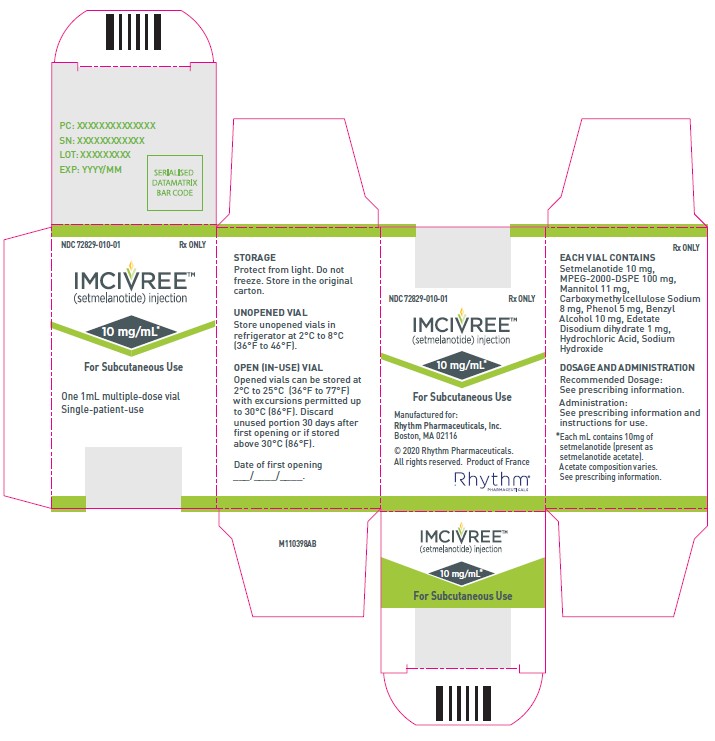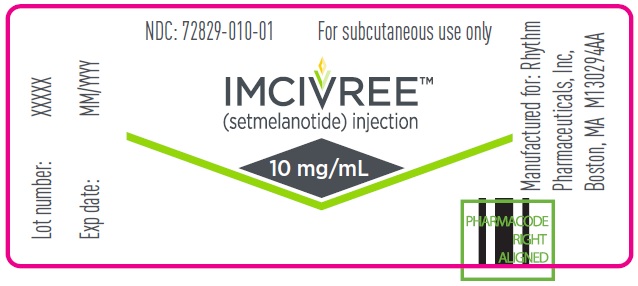 DRUG LABEL: Imcivree
NDC: 72829-010 | Form: SOLUTION
Manufacturer: Rhythm Pharmaceuticals, Inc
Category: prescription | Type: HUMAN PRESCRIPTION DRUG LABEL
Date: 20251219

ACTIVE INGREDIENTS: SETMELANOTIDE 10 mg/1 mL
INACTIVE INGREDIENTS: SODIUM N-(CARBONYL-METHOXYPOLYETHYLENE GLYCOL 2000)-1,2-DISTEAROYL-SN-GLYCERO-3-PHOSPHOETHANOLAMINE 100 mg/1 mL; MANNITOL 11 mg/1 mL; CARBOXYMETHYLCELLULOSE 8 mg/1 mL; PHENOL 5 mg/1 mL; BENZYL ALCOHOL 10 mg/1 mL; EDETATE DISODIUM 1 mg/1 mL; HYDROCHLORIC ACID; SODIUM HYDROXIDE

HIGHLIGHTS OF PRESCRIBING INFORMATION

These highlights do not include all the information needed to use IMCIVREE safely and effectively. See full prescribing information for IMCIVREE.
IMCIVREE® (setmelanotide) injection, for subcutaneous use
Initial U.S. Approval: 2020

RECENT MAJOR CHANGES

Indications and Usage (1) | 12/2024
Dosage and Administration (2.4, 2.5) | 12/2024
Warnings and Precautions (5.4) | 12/2024

1 INDICATIONS AND USAGE

IMCIVREE is a melanocortin 4 (MC4) receptor agonist indicated to reduce excess body weight and maintain weight reduction long term in adults and pediatric patients 2 years of age and older with syndromic or monogenic obesity due to:

- Bardet-Biedl syndrome (BBS). (1)
- Pro-opiomelanocortin (POMC), proprotein convertase subtilisin/kexin type 1 (PCSK1), or leptin receptor (LEPR) deficiency as determined by an FDA-approved test demonstrating variants in POMC, PCSK1, or LEPRgenes that are interpreted as pathogenic, likely pathogenic, or of uncertain significance (VUS). (1)

Limitations of Use:

IMCIVREE is notindicated for the treatment of patients with the following conditions as IMCIVREE would not be expected to be effective:

- Obesity due to suspected POMC, PCSK1, or LEPR-deficiency with POMC, PCSK1, or LEPRvariants classified as benign or likely benign. (1)
- Other types of obesity not related to BBS or POMC, PCSK1 or LEPR deficiency, including obesity associated with other genetic syndromes and general (polygenic) obesity. (1)

2 DOSAGE AND ADMINISTRATION

- Select patients for treatment who have a clinical diagnosis of BBS or who have genetically determined or suspected deficiency of POMC, PCSK1, or LEPR. (2.1)
- Recommended starting dosage injected subcutaneously for:
  - Adults and pediatric patients aged 12 years and older is 2 mg (0.2 mL) once daily for 2 weeks. (2.2)
  - Pediatric patients aged 6 to less than 12 years is 1 mg (0.1 mL) once daily for 2 weeks. (2.3)
  - Pediatric patients aged 2 to less than 6 years is 0.5 mg (0.05 mL) once daily for 2 weeks. (2.4)
- Recommended maintenance dosage for adults and pediatric patients aged 6 years and older is 3 mg (0.3 mL) injected subcutaneously once daily. (2.2, 2.3)
- Recommended maintenance dose for pediatric patients aged 2 to less than 6 years is determined by body weight. (2.4)
- For recommended dosage in patients with renal impairment, see Full Prescribing Information. (2.5)
- For titration and administration recommendations, see Full Prescribing Information. (2.2, 2.3, 2.4, 2.5, 2.6)

3 DOSAGE FORMS AND STRENGTHS

Injection: 10 mg/mL solution in a 1 mL multiple-dose vial for single patient use (3)

4 CONTRAINDICATIONS

Prior serious hypersensitivity to setmelanotide or any of the excipients in IMCIVREE (4)

5 WARNINGS AND PRECAUTIONS

- Disturbance in Sexual Arousal:Spontaneous penile erections in males and sexual adverse reactions in females have occurred. Inform patients that these events may occur and instruct patients who have an erection lasting longer than 4 hours to seek emergency medical attention. (5.1)
- Depression and Suicidal Ideation:Depression and suicidal ideation have occurred. Monitor patients for new onset or worsening depression or suicidal thoughts or behaviors. Consider discontinuing IMCIVREE if patients experience suicidal thoughts or behaviors, or clinically significant or persistent depression symptoms occur. (5.2)
- Hypersensitivity Reactions:Serious hypersensitivity reactions (e.g., anaphylaxis) have been reported. If suspected, advise patients to promptly seek medical attention and discontinue IMCIVREE. (5.3).
- Skin Hyperpigmentation, Darkening of Pre-Existing Nevi, and Development of New Melanocytic Nevi:Generalized increased skin pigmentation, darkening of pre-existing nevi, and development of new nevi have occurred. Perform a full body skin examination prior to initiation and periodically during treatment to monitor pre-existing and new pigmentary lesions. (5.4)
- Risk of Serious Adverse Reactions Due to Benzyl Alcohol Preservative in neonates and low birth weight infants:_IMCIVREE is not approved for use in neonates or infants. Serious and fatal adverse reactions including “gasping syndrome” can occur in neonates and low birth weight infants treated with benzyl alcohol-preserved drugs. (5.5)

6 ADVERSE REACTIONS

Most common adverse reactions (incidence ≥20%) included skin hyperpigmentation, injection site reactions, nausea, headache, diarrhea, abdominal pain, vomiting, depression, and spontaneous penile erection. (6.1)

To report SUSPECTED ADVERSE REACTIONS, contact Rhythm Pharmaceuticals at 1-833-789-6337 or FDA at 1-800-FDA-1088 or www.fda.gov/medwatch.

8 USE IN SPECIFIC POPULATIONS

- Lactation:not recommended when breastfeeding (8.2)

FULL PRESCRIBING INFORMATION

1 INDICATIONS AND USAGE

IMCIVREE is indicated to reduce excess body weight and maintain weight reduction long term in adults and pediatric patients aged 2 years and older with syndromic or monogenic obesity due to:

- Bardet-Biedl syndrome (BBS) [see Dosage and Administration (2.1)]
- Pro-opiomelanocortin (POMC), proprotein convertase subtilisin/kexin type 1 (PCSK1), or leptin receptor (LEPR) deficiency as determined by an FDA-approved test demonstrating variants in POMC, PCSK1, or LEPRgenes that are interpreted as pathogenic, likely pathogenic, or of uncertain significance (VUS) [see Dosage and Administration (2.1)].

Limitations of Use:

IMCIVREE is notindicated for the treatment of patients with the following conditions as
IMCIVREE would not be expected to be effective:

- Obesity due to suspected POMC, PCSK1, or LEPR deficiency with POMC, PCSK1, or LEPRvariants classified as benign or likely benign
- Other types of obesity not related to BBS or POMC, PCSK1, or LEPR deficiency, including obesity associated with other genetic syndromes and general (polygenic) obesity

2 DOSAGE AND ADMINISTRATION

2.1 Patient Selection

BBS

- Select patients for treatment with IMCIVREE who have a clinical diagnosis of BBS [see Clinical Studies (14)]. Consider genetic confirmation in pediatric patients aged <6 years.

POMC, PCSK1, or LEPR Deficiency

- Select patients for treatment with IMCIVREE who have genetically determined or suspected deficiency of POMC, PCSK1, or LEPR [see Clinical Studies (14)].
- Treat patients with variants in POMC, PCSK1, or LEPR genes that are interpreted as pathogenic, likely pathogenic, or of uncertain significance (VUS) in the clinical context of the patient [see Clinical Studies (14)].
- Information on an FDA-approved test for the detection of variants in the POMC, PCSK1,or LEPRis available at http://www.fda.gov/CompanionDiagnostics.

2.2 Recommended Dosage in Adults and Pediatric Patients Aged 12 Years and Older

- The recommended starting dosage is 2 mg (0.2 mL) injected subcutaneously once daily for 2 weeks in adults and pediatric patients aged 12 years and older.
- Monitor patients for gastrointestinal (GI) adverse reactions during dosage initiation and titration [see Adverse Reactions (6.1)] .
- If the starting dosage is:
  - Not tolerated, reduce the dosage to 1 mg (0.1 mL) once daily. If the 1 mg once daily dosage is tolerated for at least 1 week, increase the dosage to 2 mg (0.2 mL) once daily.
  - Tolerated for 2 weeks, increase the dosage to 3 mg (0.3 mL) once daily. If the 3 mg once daily dosage is not tolerated, decrease the dosage to 2 mg (0.2 mL) once daily.
- The recommended maintenance dosage is 3 mg (0.3 mL) injected subcutaneously once daily.

2.3 Recommended Dosage in Pediatric Patients Aged 6 to Less Than 12 Years

- The recommended starting dosage is 1 mg (0.1 mL) injected subcutaneously once daily for 2 weeks in pediatric patients aged 6 to less than 12 years.
- Monitor patients for GI adverse reactions during dosage initiation and titration [see Adverse Reactions (6.1)] .
- If the starting dosage is:
  - Not tolerated, reduce the dosage to 0.5 mg (0.05 mL) once daily. If the 0.5 mg once daily dosage is tolerated for at least 1 week, increase the dosage to 1 mg (0.1 mL) once daily.
  - Tolerated for 2 weeks, increase the dosage to 2 mg (0.2 mL) once daily. If the 2 mg daily dosage is:
    - Not tolerated, reduce the dosage to 1 mg (0.1 mL) once daily.
    - Tolerated, increase the dosage to 3 mg (0.3 mL) once daily.
- The recommended maintenance dosage is 3 mg (0.3 mL) injected subcutaneously once daily.

2.4 Recommended Dosage in Pediatric Patients Aged 2 to Less Than 6 Years

- The recommended starting dosage is 0.5 mg (0.05 mL) injected subcutaneously once daily for 2 weeks in pediatric patients aged 2 to less than 6 years.
- Monitor patients for GI adverse reactions during dosage initiation and titration [see Adverse Reactions (6.1)] .
- If the starting dosage is:
  - Not tolerated, discontinue the product.
  - Tolerated for 2 weeks, increase the dosage based on baseline body weight, as presented in Table 1.

Table 1:Recommended Maintenance Dosage Based on Baseline Body Weight in Pediatric Patients Aged 2 to Less Than 6 Years
Patient Weight/Treatment Week | Daily Dose | Volume to be Injected
15 kg to less than 20 kg
Week 1 and onward | 0.5 mg once daily | 0.05 mL once daily
20 kg to less than 30 kg
Weeks 1‑2 | 0.5 mg once daily | 0.05 mL once daily
Week 3 and onward | 1 mg once daily | 0.1 mL once daily
30 kg to less than 40 kg
Weeks 1‑2 | 0.5 mg once daily | 0.05 mL once daily
Weeks 3‑4 | 1 mg once daily | 0.1 mL once daily
Week 5 and onward | 1.5 mg once daily | 0.15 mL once daily
Greater than or equal to 40 kg
Weeks 1‑2 | 0.5 mg once daily | 0.05 mL once daily
Weeks 3‑4 | 1 mg once daily | 0.1 mL once daily
Weeks 5‑6 | 1.5 mg once daily | 0.15 mL once daily
Weeks 7 and onward | 2 mg once daily | 0.2 mL once daily

2.5 Recommended Dosage in Patients with Renal Impairment

Recommended Dosage in Adults and Pediatric Patients Aged 2 Years and Older with End Stage Renal Disease [estimated glomerular filtration (eGFR) less than 15 mL/min/1.73 m^2]

IMCIVREE is not recommended for use in patients with end stage renal disease.

Recommended Dosage in Patients with Severe Renal Impairment (eGFR of 15 to 29 mL/min/1.73 m^2)

Adults and Pediatric Patients Aged 12 Years and Older

- The recommended starting dosage is 0.5 mg (0.05 mL) injected subcutaneously once daily for 2 weeks in adults and pediatric patients aged 12 years and older with severe renal impairment.
- Monitor patients for GI adverse reactions during dosage initiation and titration [see Adverse Reactions (6.1)] .
- If the recommended starting dosage is [see Use in Specific Populations (8.6)] :
  - Not tolerated, discontinue IMCIVREE.
  - Tolerated for 2 weeks, increase the dosage to 1 mg (0.1 mL) once daily. If the 1 mg daily dosage is tolerated for at least 1 week, increase the dosage to 1.5 mg (0.15 mL) once daily. The recommended maintenance dosage is 1.5 mg (0.15 mL) injected subcutaneously once daily [see Use in Specific Populations (8.6) and Clinical Pharmacology (12.3)] .

Pediatric Patients Ages 6 Years to Less Than 12 Years

- The recommended starting dosage is 0.5 mg (0.05 mL) injected subcutaneously once daily for 2 weeks in pediatric patients aged 6 to less than 12 years with severe renal impairment.
- Monitor patients for GI adverse reactions during dosage initiation and titration [see Adverse Reactions (6.1)] .
- If the recommended starting dosage is [see Use in Specific Populations (8.6)] :
  - Not tolerated, discontinue IMCIVREE.
  - Tolerated for 2 weeks, increase the dosage to 1 mg (0.1 mL) injected subcutaneously once daily. The recommended maintenance dosage is 1 mg (0.1 mL) injected subcutaneously once daily

Pediatric Patients Aged 2 to Less Than 6 Years Weighing at Least 20 kg

- The recommended starting dosage is 0.5 mg (0.05 mL) injected subcutaneously once daily for 2 weeks in pediatric patients aged 2 to less than 6 years with severe renal impairment and weight of at least 20 kg.
  - The use of IMCIVREE in pediatric patients aged 2 to less than 6 years with weight less than 20 kg and severe renal impairment is not recommended [see Use in Specific Populations (8.6) and Clinical Pharmacology (12.3)] .
- Monitor patients for GI adverse reactions during dosage initiation and titration [see Adverse Reactions (6.1)] .
- If the recommended starting dosage is [see Use in Specific Populations (8.6)] :
  - Not tolerated, discontinue IMCIVREE.
  - Tolerated for 2 weeks, increase the dosage based on baseline body weight, as presented in Table 2 [see Use in Specific Populations (8.6) and Clinical Pharmacology (12.3)] .

Table 2: Recommended Maintenance Dosage Based on Baseline Body Weight in Pediatric Patients 2 to Less Than 6 Years of Age Weighing at Least 20 kg and with Severe Renal Impairment
Patient Weight/Treatment Week | Daily Dose | Volume to be Injected
20 kg to less than 30 kg
Week 1 and onward | 0.5 mg once daily | 0.05 mL once daily
30 kg to less than 40 kg
Weeks 1‑2 | 0.5 mg once daily | 0.05 mL once daily
Week 3 and onward | 1 mg once daily | 0.1 mL once daily
Greater than or equal to 40 kg
Weeks 1‑2 | 0.5 mg once daily | 0.05 mL once daily
Week 3 and onward | 1 mg once daily | 0.1 mL once daily

- The recommended maintenance dosage is 1 mg (0.1 mL) injected subcutaneously once daily [see Use in Specific Populations (8.6) and Clinical Pharmacology (12.3)] . Monitor patients for adverse reactions [see Adverse Reactions (6.1)] .

Recommended Dosage in Adults and Pediatric Patients Aged 2 Years and Older with Mild (eGFR of 60 to 89 mL/min/1.73 m^2) or Moderate (eGFR of 30 to 59 mL/min/1.73 m^2) Renal Impairment

The recommended dosage in patients with mild or moderate renal impairment is the same as in those with normal kidney function [see Dosage and Administration (2.2, 2.3, 2.4)] .

2.6 Administration Instructions

- Prior to initiation of IMCIVREE, train patients or their caregivers on proper injection technique. Instruct patients to use a 1-mL syringe with a 28-gauge or 29-gauge needle appropriate for subcutaneous injection.
- Remove IMCIVREE from the refrigerator approximately 15 minutes prior to administration. Alternatively, warm IMCIVREE prior to administration by rolling the vial gently between the palms of the hands for 60 seconds.
- Inspect IMCIVREE visually before use. It should appear clear to slightly opalescent, colorless to slightly yellow. Do not use if particulate matter or discoloration is seen.
- Administer IMCIVREE once daily, at the beginning of the day, without regard to meals.
- Inject IMCIVREE subcutaneously in the abdomen, thigh, or arm, rotating to a different site each day. Do not administer IMCIVREE intravenously or intramuscularly.
- If a dose is missed, resume the once daily regimen as prescribed with the next scheduled dose.

3 DOSAGE FORMS AND STRENGTHS

Injection: 10 mg/mL, clear to slightly opalescent, colorless to slightly yellow solution in a 1-mL multiple-dose vial for single patient use.

4 CONTRAINDICATIONS

IMCIVREE is contraindicated in patients with a prior serious hypersensitivity reaction to setmelanotide or any of the excipients in IMCIVREE. Serious hypersensitivity reactions have included anaphylaxis [see Warnings and Precautions (5.3)].

5 WARNINGS AND PRECAUTIONS

5.1 Disturbance in Sexual Arousal

Sexual adverse reactions may occur in patients treated with IMCIVREE. Spontaneous penile erections in males (24% in patients aged 6 years and older; 8% in patients aged 2 to less than 6 years) and sexual adverse reactions in females (7% in IMCIVREE-treated patients aged 6 years and older and 0% in placebo-treated patients from an unapproved population) occurred in clinical studies with IMCIVREE [see Adverse Reactions (6.1)].

Inform patients that these events may occur and instruct patients who have an erection lasting longer than 4 hours to seek emergency medical attention.

5.2 Depression and Suicidal Ideation

Some drugs that target the central nervous system, such as IMCIVREE, may cause depression or suicidal ideation. Depression (26% in patients aged 6 years and older), suicidal ideation (11% in patients aged 6 years and older), and depressed mood (8% in patients aged 2 to less than 6 years) occurred in adults and pediatric patients in IMCIVREE clinical studies [see Adverse Reactions (6.1)]. Patients with a history of depression or suicidal ideation may be at increased risk for recurrent episodes while taking IMCIVREE.

Monitor patients for new onset or worsening of depression, suicidal thoughts or behavior, or any unusual changes in mood or behavior. Consider discontinuing IMCIVREE if patients experience suicidal thoughts or behaviors or if clinically significant or persistent depression symptoms occur.

5.3 Hypersensitivity Reactions

Serious hypersensitivity reactions, including anaphylaxis, have been reported with IMCIVREE. These reactions generally occurred within minutes to hours after injecting IMCIVREE [see Adverse Reactions (6.2)]. If hypersensitivity reactions occur, advise patients to promptly seek medical attention and discontinue use of IMCIVREE. IMCIVREE is contraindicated in patients with a prior serious hypersensitivity reaction to setmelanotide or any of the excipients in IMCIVREE.

5.4 Skin Hyperpigmentation, Darkening of Pre-Existing Nevi, and Development of New Melanocytic Nevi

Generalized or focal increases in skin pigmentation occurred in the majority of patients (67% in patients aged 6 years and older; 83% in patients 2 to less than 6 years) treated with IMCIVREE in clinical trials [see Adverse Reactions (6.1) and Clinical Pharmacology (12.1)]. This effect is reversible upon discontinuation of the drug.

IMCIVREE may also cause the development of new melanocytic nevi or darkening of pre-existing nevi due to its pharmacologic effect. Development of new melanocytic nevi and darkening or increase in size of existing melanocytic nevi occurred in 16% of patients aged 6 years and older and 33% of patients aged 2 to less than 6 years.

Perform a full body skin examination prior to initiation and periodically during treatment with IMCIVREE to monitor pre-existing and new skin pigmented lesions

5.5 Risk of Serious Adverse Reactions Due to Benzyl Alcohol Preservative in Neonates and Low Birth Weight Infants

IMCIVREE is not approved for use in neonates or infants. Serious and fatal adverse reactions including “gasping syndrome” can occur in neonates and low birth weight infants treated with benzyl alcohol-preserved drugs, including IMCIVREE. The “gasping syndrome” is characterized by central nervous system depression, metabolic acidosis, and gasping respirations. The minimum amount of benzyl alcohol at which serious adverse reactions may occur is not known (IMCIVREE contains 10 mg of benzyl alcohol per mL) [see Use in Specific Populations (8.4)].

6 ADVERSE REACTIONS

The following clinically significant adverse reactions are described elsewhere in the labeling:

- Disturbance in Sexual Arousal [see Warnings and Precautions (5.1)]
- Depression and Suicidal Ideation [see Warnings and Precautions (5.2)]
- Hypersensitivity Reactions [see Warnings and Precautions (5.3)]
- Skin Hyperpigmentation, Darkening of Pre-Existing Nevi, and Development of New Melanocytic Nevi [see Warnings and Precautions (5.4)]

6.1 Clinical Trials Experience

Because clinical trials are conducted under widely varying conditions, adverse reaction rates observed in the clinical trials of a drug cannot be directly compared to rates in the clinical trials of another drug and may not reflect the rates observed in practice.

Bardet-Biedl Syndrome (Adults and Pediatric Patients Aged 6 Years and Older)

The safety of IMCIVREE was evaluated in a clinical study, which included a 14 week, randomized, double-blind, placebo-controlled period followed by a 52-week open-label, treatment period, in 44 patients aged 6 years and older with obesity and a clinical diagnosis of BBS (Study 1) [see Clinical Studies (14)]. The study duration was 66 weeks.

During the 14-week placebo-controlled period in Study 1, the most common reported adverse reactions in IMCIVREE-treated patients when compared to placebo-treated patients were hyperpigmentation disorders (67% vs 0%, respectively) and vomiting (11% vs 0%, respectively).

Adverse reactions were also evaluated during the 52-week active-treatment period, defined as the period from randomization to Week 52 in patients initially randomized to IMCIVREE, and from Week 14 to Week 66 in patients initially randomized to placebo. Table 3summarizes the adverse reactions that occurred in 2 or more IMCIVREE-treated patients in Study 3 during the 52-week active treatment period.

Table 3: Adverse Reactions Occurring in 2 or More IMCIVREE-Treated Patients with Obesity and a Clinical Diagnosis of BBS During the 52-week Active-Treatment Period from the Start of IMCIVREE Treatment (Study 1)
Adverse Reaction | IMCIVREE-treated Patients N = 43^1 %
Skin hyperpigmentation^2 | 63
Injection Site Reactions^3 | 51
Nausea | 26
Spontaneous penile erection^4 | 25
Vomiting | 19
Diarrhea | 14
Melanocytic nevus^5 | 14
Headache | 7
Skin striae | 7
Aggression | 5
Fatigue | 5
^143 patients were treated with at least 1 dose of IMCIVREE; 1 patient initially randomized to placebo withdrew from the study prior to receiving IMCIVREE and is not included
^2Includes skin hyperpigmentation, hair color changes, melanoderma
^3Includes injection site erythema, pruritis, induration, pain, bruising, edema, reaction, hemorrhage, irritation, mass
^4n = 20 male patients
^5Includes new melanocytic nevus formation, increased melanocytic nevus size, and darkening of pre-existing melanocytic nevus

POMC, PCSK1, and LEPR Deficiency (Adults and Pediatric Patients Aged 6 Years and Older)

The safety of IMCIVREE was evaluated in two 52-week, open-label clinical studies of 27 patients aged 6 years and older with obesity due to POMC, PCSK1, or LEPR deficiency with POMC, PCSK1, or LEPR genes that are interpreted as pathogenic, likely pathogenic, or of uncertain significance (Study 2 and Study 3) [see Clinical Studies (14)] .

Table 4summarizes the adverse reactions that occurred in the open-label studies during the first 52 weeks of treatment in 3 or more patients treated with IMCIVREE.

Table 4: Adverse Reactions Occurring in 3 or More IMCIVREE-Treated Patients Aged 6 Years and Older with Obesity due to POMC, PCSK1, or LEPR Deficiency in Open-Label Clinical Studies of 52-Week Duration (Study 2 and Study 3)
Adverse Reaction | IMCIVREE-treated Patients N = 27 %
Injection site reaction^1 | 96
Skin hyperpigmentation^2 | 78
Nausea | 56
Headache | 41
Diarrhea | 37
Abdominal pain^3 | 33
Back pain | 33
Fatigue | 30
Vomiting | 30
Depression^4 | 26
Upper respiratory tract infection | 26
Spontaneous penile erection^5 | 23
Arthralgia | 19
Asthenia | 19
Melanocytic nevus^6 | 19
Dizziness | 15
Dry mouth | 15
Dry skin | 15
Insomnia | 15
Vertigo | 15
Alopecia | 11
Chills | 11
Constipation | 11
Influenza-like illness | 11
Muscle spasm | 11
Pain in extremity | 11
Rash | 11
Suicidal ideation | 11
^1Includes injection site erythema, pruritus, edema, pain, induration, bruising, injection site hypersensitivity, hematoma, nodule, and discoloration
^2Includes skin hyperpigmentation, pigmentation disorders, skin discoloration, gingival discoloration
^3Includes abdominal pain and upper abdominal pain
^4Includes depressed mood
^5n = 13 male patients
^6Includes new melanocytic nevus formation, increased melanocytic nevus size, and darkening of pre-existing melanocytic nevus

POMC, PCSK1, and LEPR Deficiency and BBS (Pediatric Patients Aged 2 to <6 Years)

The safety of IMCIVREE was evaluated in one 52-week, open-label clinical study of 12 patients aged 2 to less than 6 years with obesity due to POMC, PCSK1, or LEPR deficiency with POMC, PCSK1,or LEPRgenes that are interpreted as pathogenic, likely pathogenic, or of uncertain significance, or obesity due to BBS (Study 4) [see Clinical Studies (14)] . No patients with PCSK1 were enrolled in the trial.

Table 5summarizes the adverse reactions that occurred in the open-label study during 52 weeks of treatment in 3 or more patients treated with IMCIVREE.

Table 5: Adverse Reactions Occurring in 3 or More IMCIVREE-Treated Patients Aged 2 to <6 Years with Obesity due to POMC or LEPR Deficiency or BBS in an Open-Label Clinical Study of 52-Week Duration (Study 4)
Adverse Reaction | IMCIVREE-treated Patients N = 12 %
Skin hyperpigmentation^1 | 83
Injection Site Reactions^2 | 67
Vomiting | 58
Nasopharyngitis | 42
Melanocytic nevus^3 | 33
Fall | 33
Fever | 33
Upper respiratory tract infection | 33
Cough | 25
Diarrhea | 25
^1Includes skin hyperpigmentation, ephelides, nail pigmentation, pigmentation lip, skin discoloration, gingival hyperpigmentation
^2Includes injection site bruising, pruritus, discoloration, erythema, induration, oedema, pain, urticaria
^3Includes new melanocytic nevus formation, increased melanocytic nevus size, and darkening of pre-existing melanocytic nevus

6.2 Postmarketing Experience

The following adverse reactions have been identified during post-approval use of IMCIVREE. Because these reactions are reported voluntarily from a population of uncertain size, it is not always possible to reliably estimate their frequency or establish a causal relationship to drug exposure.

- Hypersensitivity, including anaphylaxis

8 USE IN SPECIFIC POPULATIONS

8.1 Pregnancy

Risk Summary

Discontinue IMCIVREE when pregnancy is recognized unless the benefits of therapy outweigh the potential risks to the fetus.

IMCIVREE contains the preservative benzyl alcohol. Because benzyl alcohol is rapidly metabolized by a pregnant woman, benzyl alcohol exposure in the fetus is unlikely. However, adverse reactions have occurred in premature neonates and low birth weight infants who received intravenously administered benzyl alcohol-containing drugs [see Warnings and Precautions (5.5) and Use in Specific Populations (8.4)].

There are no available data with IMCIVREE in pregnant women to inform a drug-associated risk for major birth defects and miscarriage, or adverse maternal or fetal outcomes. For the general US population, weight loss offers no potential benefit to a pregnant woman and may result in fetal harm (see Clinical Considerations) . In animal reproduction studies, setmelanotide subcutaneously administered to pregnant rats from before mating to the end of organogenesis was not teratogenic at doses 11 times the maximum recommended human dose (MRHD) of 3 mg. Setmelanotide subcutaneously administered to pregnant rabbits during the period of organogenesis was not teratogenic at clinical doses. Setmelanotide administered subcutaneously to pregnant rats during organogenesis through lactation did not result in adverse developmental effects at doses 7 times the MRHD (see Data).

The estimated background risk of birth defects and miscarriage for the indicated population is unknown. In the U.S. general population, the estimated background risk of major birth defects and miscarriage in clinically recognized pregnancies is 2-4% and 15-20%, respectively.

Clinical Considerations

Disease-Associated Maternal and/or Embryo/Fetal Risks

Maternal obesity increases the risk for congenital malformations, including neural tube defects, cardiac malformations, oral clefts, and limb reduction defects. In addition, weight loss during pregnancy may result in fetal harm including increased risk of small for gestational age. Appropriate weight gain based on pre-pregnancy weight is currently recommended for all pregnant women, including those who are already overweight or have obesity, due to the obligatory weight gain that occurs in maternal tissues during pregnancy.

Data

Animal Data

Embryo-fetal development was evaluated in female rats administered setmelanotide subcutaneously during mating to end of major organogenesis (14 days prior to mating to gestation day 17) at doses of 0.5, 3, and 5 mg/kg/day, resulting in exposures up to 11 times the human exposure at MRHD of 3 mg, based on AUC. Dose-related decreases in maternal food intake and body weight gain were observed during the premating period but not during gestation. No evidence of embryo-fetal toxicity was observed.

Embryo-fetal development was evaluated in pregnant rabbits subcutaneously administered setmelanotide during organogenesis (gestation days 7 to 19) at doses of 0.05, 0.1, and 0.2 mg/kg/day, resulting in clinically relevant exposures at the MRHD, based on AUC. Decreases in maternal food consumption and body weight were observed at all doses. Increases in embryo-fetal resorptions and post-implantation losses were observed at ≥0.1 mg/kg/day in the presence of significant maternal toxicity, and fetal body weights were 7% lower than controls at 0.2 mg/kg/day.

Pre- and post-natal development was evaluated in rats subcutaneously administered setmelanotide during organogenesis and continuing until weaning (gestation day 6 to lactation day 21) at doses of 0.5, 3.0, and 5.0 mg/kg/day, which resulted in exposures up to 7 times the human exposure at the MRHD, based on AUC. Pup body weights at birth were 9% lower than controls at 3.0 and 5.0 mg/kg/day, which was consistent with reduced maternal body weight gain and food consumption during gestation. No adverse setmelanotide-related effects on pup survival, growth, maturation, visual function, neurobehavioral performance, or reproductive performance were observed up to the highest dose.

8.2 Lactation

Risk Summary

Treatment with IMCIVREE is not recommended for use while breastfeeding.

IMCIVREE from multiple-dose vials contains the preservative benzyl alcohol. Because benzyl alcohol is rapidly metabolized by a lactating woman, benzyl alcohol exposure in the breastfed infant is unlikely. However, adverse reactions have occurred in premature neonates and low birth weight infants who received intravenously administered benzyl alcohol-containing drugs [see Warnings and Precautions (5.5) and Use in Specific Populations (8.4)] .

There is no information on the presence of setmelanotide or its metabolites in human milk, the effects on the breastfed infant, or the effects on milk production. However, setmelanotide is present in the milk of rats (see Data). When a drug is present in rat milk, it is likely that the drug will be present in human milk.

Data

Dose-related setmelanotide concentrations were observed in milk 2 hours after subcutaneous injection in the preweaning phase of a pre- and post-natal development study in rats. No quantifiable setmelanotide concentrations were detected in plasma from nursing pups on post-natal Day 11.

8.4 Pediatric Use

The safety and effectiveness of IMCIVREE have been established to reduce excess body weight and maintain weight reduction long term in pediatric patients aged 2 years and older with obesity due to:

- BBS [see Clinical Studies (14.1)]
- POMC, PCSK1, or LEPR deficiency with variants in POMC, PCSK1,or LEPRgenes that are interpreted as pathogenic, likely pathogenic, or of uncertain significance (VUS) [see Clinical Studies (14.2)]

Use of IMCIVREE for these indications is supported by evidence from one 66-week study, which included a 14-week, randomized, double-blind, placebo-controlled period followed by a 52-week open-label period, and included 22 pediatric patients with BBS aged 6 to 17 years (Study 1); from two 1-year, open-label studies that included 9 pediatric patients with POMC, PCSK1, or LEPR deficiency aged 6 to 17 years (Study 2 and Study 3); and one 1-year, open-label study that included 12 pediatric patients with POMC or LEPR deficiency or BBS aged 2 to less than 6 years (Study 4) [see Clinical Studies (14.1, 14.2, 14.3)] .

Adverse reactions with IMCIVREE treatment in pediatric patients aged 2 to less than 6 years were generally similar to those reported in adults and in pediatric patients aged 6 years and older. Pediatric patients treated with IMCIVREE had greater incidences of vomiting, skin hyperpigmentation, and new or darkening nevi compared to adults treated with IMCIVREE [see Adverse Reactions (6.1)] . Perform a full body skin examination prior to initiation and periodically during treatment with IMCIVREE to monitor pre-existing and new skin pigmented lesions. [see Warnings and Precautions (5.4)]

The safety and effectiveness of IMCIVREE have not been established in pediatric patients younger than 2 years of age.

IMCIVREE is not approved for use in neonates or infants. Serious adverse reactions including fatal reactions and the “gasping syndrome” occurred in premature neonates and low birth weight infants in the neonatal intensive care unit who received drugs containing benzyl alcohol as a preservative. In these cases, benzyl alcohol dosages of 99 to 234 mg/kg/day produced high levels of benzyl alcohol and its metabolites in the blood and urine (blood levels of benzyl alcohol were 0.61 to 1.378 mmol/L). Additional adverse reactions included gradual neurological deterioration, seizures, intracranial hemorrhage, hematologic abnormalities, skin breakdown, hepatic and renal failure, hypotension, bradycardia, and cardiovascular collapse. Preterm, low-birth weight infants may be more likely to develop these reactions because they may be less able to metabolize benzyl alcohol. The minimum amount of benzyl alcohol at which serious adverse reactions may occur is not known (IMCIVREE contains 10 mg of benzyl alcohol) [see Warnings and Precautions (5.5)] .

8.5 Geriatric Use

Clinical studies of IMCIVREE did not include patients aged 65 and over. It is not known whether geriatric patients would respond differently than younger adult patients.

8.6 Renal Impairment

Patients with severe renal impairment have a higher exposure of setmelanotide relative to patients with normal kidney function. Reduce the recommended starting and maintenance dosage of IMCIVREE in adults and pediatric patients 2 years of age and older with severe renal impairment (eGFR 15 29 mL/min/1.73 m^2). The use of IMCIVREE in pediatric patients aged 2 to less than 6 years with weight less than 20 kg and severe renal impairment is not recommended [see Dosage and Administration (2.5), Clinical Pharmacology (12.3)].

The recommended dosage in patients with mild (eGFR of 60-89 mL/min/1.73 m^2) or moderate renal impairment (eGFR of 30-59 mL/min/1.73 m^2) is the same as those with normal kidney function [see Clinical Pharmacology (12.3)].

IMCIVREE is not recommended for use in patients with end stage renal disease (eGFR less than 15 mL/min/1.73 m^2).

10 OVERDOSAGE

In the event of an overdose initiate appropriate supportive treatment according to the patient’s clinical signs and symptoms.

11 DESCRIPTION

IMCIVREE contains setmelanotide acetate, a melanocortin 4 (MC4) receptor agonist. Setmelanotide is an 8 amino acid cyclic peptide analog of endogenous melanocortin peptide α-MSH (alpha-melanocyte stimulating hormone).

The chemical name for setmelanotide acetate is acetyl-L-arginyl-L-cysteinyl-D-alanyl-L-histidinyl-D-phenylalanyl-L-arginyl-L-tryptophanyl-L-cysteinamide cyclic (2→8)-disulfide acetate. Its molecular formula is C49H68N18O9S2(anhydrous, free-base), and molecular mass is 1117.3 Daltons (anhydrous, free-base).

The chemical structure of setmelanotide acetate is:

IMCIVREE (setmelanotide) injection is a sterile clear to slightly opalescent, colorless to slightly yellow solution for subcutaneous use. Each 1 mL single-patient use vial of IMCIVREE contains 10 mg of setmelanotide provided as setmelanotide acetate, which is a salt with 2 to 4 molar equivalents of acetate, and the following inactive ingredients: 10 mg benzyl alcohol, 8 mg carboxymethylcellulose sodium (average MWt 90,500), 1 mg edetate disodium dihydrate, 100 mg N-(carbonyl-methoxypolyethylene glycol 2000)-1,2-distearoyl- glycero-3- phosphoethanolamine sodium salt, 11 mg mannitol, 5 mg phenol, hydrochloric acid, sodium hydroxide and Water for Injection. The pH of IMCIVREE is 5 to 6.

12 CLINICAL PHARMACOLOGY

12.1 Mechanism of Action

Setmelanotide is an MC4 receptor agonist with 20-fold less activity at the melanocortin 3 (MC3) and melanocortin 1 (MC1) receptors. MC4 receptors in the brain are involved in regulation of hunger, satiety, and energy expenditure. Based on nonclinical evidence, setmelanotide may re-establish MC4 receptor pathway activity to reduce food intake and promote weight loss through decreased caloric intake and increased energy expenditure in patients with obesity due to BBS or POMC, PCSK1, or LEPR deficiency associated with insufficient activation of the MC4 receptor. The MC1 receptor is expressed on melanocytes, and activation of this receptor leads to accumulation of melanin and increased skin pigmentation independently of ultraviolet light [see Warnings and Precautions (5.4) and Adverse Reactions (6.1)] .

12.2 Pharmacodynamics

At a dose 2.3 times the maximum recommended dose, IMCIVREE does not prolong the QT interval to any clinically relevant extent.

Energy Expenditure

Short-term administration of IMCIVREE in 12 otherwise healthy patients with obesity increased resting energy expenditure and shifted substrate oxidation to fat. The safety and effectiveness of IMCIVREE have not been established in such patients and IMCIVREE is not approved to treat such patients [see Indications and Usage (1)].

12.3 Pharmacokinetics

The mean steady state setmelanotide Cmax,ss, AUCtau, and trough concentration for a 3-mg dose administered subcutaneously once daily was 31 ng/mL, 373 h*ng/mL, and 5 ng/mL, respectively simulated using individual PK model parameters from 109 adult patients with normal renal function. Steady-state plasma concentrations of setmelanotide were achieved within 2 days with daily dosing of 1-3 mg setmelanotide. The accumulation of setmelanotide in the systemic circulation during once-daily dosing over 12 weeks was approximately 30%. Setmelanotide AUC and Cmaxincreased proportionally following multiple-dose subcutaneous administration in the proposed dose range (1-3 mg).

Absorption

After subcutaneous injection of IMCIVREE, plasma concentrations of setmelanotide reached maximum concentrations at a median tmaxof 8 h after dosing.

Distribution

The mean apparent volume of distribution of setmelanotide after subcutaneous administration of IMCIVREE 3 mg once daily was estimated to be 75.2 L. Protein binding of setmelanotide is 79.1%.

Elimination

The effective elimination half-life (t½) of setmelanotide was approximately 11 hours. The total apparent steady state clearance of setmelanotide following subcutaneous administration of IMCIVREE 3 mg once daily was estimated to be 7.15 L/h in a typical male patient weighing 120 kg (actual body weight) with normal renal function.

Metabolism

Setmelanotide is expected to be metabolized into small peptides by catabolic pathways.

Excretion

Approximately 39% of the administered setmelanotide dose was excreted unchanged in urine during the 24-hour dosing interval following subcutaneous administration of 3 mg once daily.

Specific Populations

No clinically significant differences in the pharmacokinetics of setmelanotide were observed based on sex or disease. The effect of age 65 years or older, pregnancy, or hepatic impairment on the pharmacokinetics of setmelanotide is unknown.

Pediatric Patients

IMCIVREE has been evaluated in pediatric patients aged 2 to less than 6 years, 6 to less than 12 years, and aged 12 to 17 years. Simulations were performed using population pharmacokinetic analysis for pediatric patients aged 2 to less than 6 years, following the maximum recommended doses in each of the body weight groups - 2 mg, 1.5 mg, 1 mg, and 0.5 mg in patients weighing ≥40 kg, 30 to <40 kg, 20 to <30 kg, and 15 to <20 kg, respectively. The analyses suggest that AUC and Cmaxin pediatric patients aged 2 to less than 6 years are 52% and 75% higher in patients weighing ≥40 kg, 45% and 63% higher in patients weighing 30 to <40 kg, 24% and 38% higher in patients weighing 20 to <30 kg, and 17% and 14% lower in patients weighing 15 to <20 kg as compared to patients greater than or equal to 18 years (3 mg dose). For patients aged 6 to less than 12 years, the setmelanotide AUC and Cmaxwere 88% and 89% higher compared to patients greater than or equal to 18 years. For patients aged 12 to 17 years, the setmelanotide AUC and Cmax were both 26% higher as compared to patients greater than or equal to 18 years [see Dosage and Administration (2.2, 2.3, 2.4)] .

Patients with Renal Impairment

Exposure parameters, AUC0-tand AUC0-inf, were approximately 13%-15%, 34%-35%, and 86%-96% higher for patients with mild, moderate, and severe renal impairment, respectively, as compared to patients with normal renal function [see Dosage and Administration (2.5)].

Renal impairment did not appear to affect plasma protein binding. The average fraction unbound (fu) was approximately 0.2 and was independent of renal function.

Drug Interaction Studies

In vitro assessment of drug-drug interactions

Setmelanotide has low potential for pharmacokinetic drug-drug interactions related to cytochrome P450 (CYP), transporters and plasma protein binding.

In vivo assessment of drug-drug interactions

No clinical studies evaluating the drug-drug interaction potential of setmelanotide have been conducted.

12.6 Immunogenicity

The observed incidence of anti-drug antibodies (ADA) is highly dependent on the sensitivity and specificity of the assay. Differences in assay methods preclude meaningful comparisons of the incidence of ADA in the studies described below with the incidence of ADA in other studies, including those of setmelanotide or of other setmelanotide products.

In patients with BBS or in patients with POMC, PCSK1, or LEPR deficiency , there is insufficient information to characterize the ADA response to setmelanotide and the effects of ADA on pharmacokinetics, pharmacodynamics, safety, or effectiveness of setmelanotide products.

During the 1-year treatment period in Study 3 in patients with obesity due to LEPR deficiency [see Clinical Studies (14.2)], 3/7 (43%) of IMCIVREE-treated patients developed antibodies to endogenous alpha-melanocyte stimulating hormone (MSH). Of these 3 patients, 2 tested positive post-IMCIVREE treatment and 1 was positive pre-treatment. Because of the limited sample size, the effect of these antibodies on the pharmacokinetics, pharmacodynamics, safety, and/or effectiveness of setmelanotide products or consequences from these antibodies against endogenous alpha-MSH could not be determined. None of the IMCIVREE-treated patients with POMC-deficiency developed antibodies to alpha-MSH.

13 NONCLINICAL TOXICOLOGY

13.1 Carcinogenesis, Mutagenesis, Impairment of Fertility

Setmelanotide was not carcinogenic in Tg.rasH2 mice at doses up to 10 mg/kg/day when given subcutaneously for 26 weeks.

Setmelanotide was not mutagenic or clastogenic in a bacterial reverse mutation test, an in vitrochromosome aberration test in human lymphocyte cultures, or an in vivobone marrow micronucleus study in rats.

There were no effects on the fertility of male rats subcutaneously administered up to 3.0 mg/kg/day setmelanotide, which represents 9 times the MRHD of 3 mg, based on AUC. No effects on the fertility of female rats were observed with subcutaneous administration up to 5 mg/kg/day setmelanotide, which represents 11 times the MRHD of 3 mg, based on AUC.

14 CLINICAL STUDIES

14.1 Bardet-Biedl Syndrome (Adults and Pediatric Patients Aged 6 Years and Older)

The safety and efficacy of IMCIVREE for weight reduction in adults and pediatric patients aged 6 years and older with obesity and a clinical diagnosis of Bardet-Biedl syndrome (BBS) were assessed in a 66-week clinical study, which included a 14 week randomized, double-blind, placebo-controlled period and a 52-week open-label period (Study 1 [ NCT03746522]). The study enrolled patients aged 6 years and above with obesity and a clinical diagnosis of BBS. Adult patients had a BMI of ≥30 kg/m^2and pediatric patients had weight ≥97thpercentile using growth chart assessments.

In Study 1, eligible patients entered a 14-week, randomized, double-blind, placebo-controlled treatment period (Period 1) in which patients received IMCIVREE or placebo, followed by a 52-week open-label treatment period (Period 2) in which all patients received IMCIVREE. To maintain the blind during Period 1, dose titration to a fixed dose of 3 mg given subcutaneously once daily was performed during the first 2 weeks of both Period 1 and Period 2.

Efficacy analyses were conducted in 44 patients at the end of Period 1 (Week 14, placebo-controlled data) and in 31 patients during the active-treatment period, defined as the period from randomization to Week 52 in patients initially randomized to IMCIVREE, and from Week 14 to Week 66 in patients initially randomized to placebo. Analyses of the active-treatment period include patients who had either completed 52 weeks from the start of IMCIVREE treatment or discontinued the study early at the time of the prespecified data cutoff.

A total of 44 patients with obesity and a clinical diagnosis of BBS were enrolled; 50% were adults, 32% were aged 12 to <18 years, and 18% were aged 6 to <12 years; 46% were male; 77% were White, 5% were Black or African American, 2% were Asian, and 16% had an unknown or not reported race; 2% were Hispanic or Latino ethnicity and 14% had an unknown or not reported ethnicity; and the mean BMI was 41.5 kg/m^2(range: 24.4-66.1 kg/m^2) at baseline.

Effect of IMCIVREE on BMI in Patients with Obesity and a Clinical Diagnosis of BBS

In patients aged ≥6 years with obesity and a clinical diagnosis of BBS in Study 1, the mean percent change in BMI after 52 weeks of IMCIVREE treatment was -7.9% (Table 6), 61.3% of patients achieved a ≥5% BMI decrease from baseline, and 38.7% had a ≥10% decrease in BMI (Table 7).

Table 6: Percent Change from Baseline in BMI after 52 Weeks from the Start of IMCIVREE Treatment in Patients Aged ≥6 Years with Obesity and a Clinical Diagnosis of BBS (Study 1)*

Statistic | Result
Baseline BMI (kg/m^2)
Mean (SD) | 41.8 (9.0)
Median | 41.5
Min, Max | 24.4, 61.3
BMI after 52 Weeks (kg/m^2)
Mean (SD) | 38.6 (9.2)
Median | 39.1
Min, Max | 20.4, 60.9
95% CI | 35.2, 41.9
Percent Change from Baseline to 52 Weeks (%)
Mean (SD) | -7.9 (6.7)
Median | -8.8
Min, Max | -25.4, 5.3
95% CI | -10.4, -5.5
Abbreviations: CI = confidence interval; SD = standard deviation
*BBS patients (N=31) who completed 52 weeks from the start of IMCIVREE treatment or discontinued the study early. Five patients who discontinued study early were defined as 0 percent change.

Table 7: Proportion of IMCIVREE-Treated Patients Aged ≥6 Years with Obesity and a Clinical Diagnosis of BBS Who Achieved at Least 5% and 10% BMI Decrease from Baseline After 52 Weeks from the Start of IMCIVREE Treatment (Study 1)
Parameter | Statistic | Result
Patients* Achieving at Least 5% BMI Loss at 52 Weeks | % | 61.3
Patients* Achieving at Least 5% BMI Loss at 52 Weeks | 95% CI | 42.2, 78.2
Patients* Achieving at Least 10% BMI Loss at 52 Weeks | % | 38.7
Patients* Achieving at Least 10% BMI Loss at 52 Weeks | 95% CI | 21.8, 57.8
Abbreviations: CI = confidence interval; SD = standard deviation
*BBS patients (N=31) who completed 52 weeks from the start of IMCIVREE treatment or discontinued the study early. Five patients who discontinued study early were defined as not achieving 5% or 10% reduction.

During the 14-week double-blind, placebo-controlled portion of Study 1 (Period 1), there was a statistically significant difference in BMI reduction between the IMCIVREE-treated group and the placebo-treated group (Table 8).

Table 8. Percent Change from Baseline in BMI after 14 Weeks of Treatment in Patients Aged ≥6 Years with Obesity and a Clinical Diagnosis of BBS (Study 1)*

Parameter | IMCIVREE (N = 22) | Placebo (N = 22)
Baseline BMI (SD) | 41.4 (10.0) | 41.6 (10.1)
BMI at 14 Weeks (SD) | 39.5 (9.9) | 41.6 (9.9)
Percent Change from Baseline to 14 Weeks (SD) | -4.6 (4.1) | -0.1 (2.3)
Placebo-Adjusted Difference | -4.5
95% CI | -6.5, -2.5
Abbreviations: CI = confidence interval; SD = standard deviation
*BBS subjects who completed the 14-week double-blind, placebo-controlled period (N=44).

Effect of IMCIVREE on Hunger in Patients with Obesity and a Clinical Diagnosis of BBS

In Study 1, patients 12 years and older who were able to self-report their hunger (n=14), recorded their daily maximal hunger in a diary, which was then assessed by the Daily Hunger Questionnaire Item 2. Hunger was scored on an 11-point scale from 0 (“not hungry at all”) to 10 (“hungriest possible”). Weekly means of daily maximal hunger scores after 52 weeks from the start of IMCIVREE treatment are summarized in Table 9.

Hunger scores decreased in IMCIVREE-treated patients during the 14-week placebo-controlled period and during the open-label treatment period.

Table 9: Daily Hunger Scores – Change from Baseline in IMCIVREE-Treated Patients Aged ≥12 Years with Obesity and a Clinical Diagnosis of BBS After 52 Weeks From the Start of IMCIVREE Treatment (Study 1)

Timepoint | Statistic | Result
Baseline | N | 14
Baseline | Mean (SD) | 6.99 (1.893)
Baseline | Median | 7.29
Baseline | Min, Max | 4.0, 10.0
Week 52 | N | 14
Week 52 | Mean (SD) | 4.87 (2.499)
Week 52 | Median | 4.43
Week 52 | Min, Max | 2.0, 10.0
Change at Week 52 | N | 14
Change at Week 52 | Mean (SD) | -2.12 (2.051)
Change at Week 52 | Median | -1.69
Change at Week 52 | Min, Max | -6.7, 0.0
Abbreviations: BBS = Bardet-Biedl syndrome; CI=confidence interval; Max=maximum; Min=minimum; NC=Not calculated; SD=Standard Deviation.
Note: Baseline is the last assessment prior to initiation of setmelanotide in both studies.
Note: The Daily Hunger Questionnaire is not administered to patients <12 years or to patients with cognitive impairment as assessed by the Investigator.

Supportive of IMCIVREE’s effect on weight loss, there were general numeric improvements in blood pressure, lipids, and waist circumference. However, because of the limited number of patients studied and the lack of a control group, the treatment effects on these parameters could not be accurately quantified.

14.2 POMC, PCSK1, and LEPR Deficiency (Adults and Pediatric Patients Aged 6 Years and Older)

The safety and efficacy of IMCIVREE for weight reduction in adults and pediatric patients 6 years of age and older with obesity due to POMC, PCSK1, or LEPR deficiency were assessed in 2 identically designed, 1-year, open-label studies, each with an 8 week, double-blind withdrawal period.

- Study 2 (NCT02896192) enrolled patients aged 6 years and above with obesity and genetically confirmed or suspected POMC or PCSK1 deficiency.
- Study 3 (NCT03287960) enrolled patients aged 6 years and above with obesity and genetically confirmed or suspected LEPR deficiency.

The studies enrolled patients with homozygous or presumed compound heterozygous pathogenic, likely pathogenic variants, or VUS for either the POMC or PCSK1genes (Study 2) or the LEPRgene (Study 3). In both studies, the local genetic testing results were centrally confirmed using Sanger sequencing. Patients with double heterozygous variants in 2 different genes were not eligible for treatment with IMCIVREE. In both studies, adult patients had a body mass index (BMI) of ≥30 kg/m^2. Weight in pediatric patients was ≥95thpercentile using growth chart assessments.

IMCIVREE dose titration occurred over a 2- to 12-week period, followed by a 10-week, open-label treatment period with IMCIVREE. Patients who achieved at least a 5-kilogram weight loss (or at least 5% weight loss if baseline body weight was <100 kg) at the end of the open-label treatment period continued into a double-blind withdrawal period lasting 8 weeks, including 4 weeks of IMCIVREE followed by 4 weeks of placebo (investigators and patients were blinded to this sequence). Following the withdrawal sequence, patients re-initiated treatment with IMCIVREE at their therapeutic dose for up to 32 weeks.

Efficacy analyses were conducted in 21 patients (10 in Study 2 and 11 in Study 3) who had completed at least 1 year of treatment at the time of a prespecified data cutoff. Six additional patients enrolled in the studies (4 in Study 2 and 2 in Study 3) who had not yet completed 1 year of treatment at the time of the cutoff were not included in the efficacy analyses.

Of the 21 patients included in the efficacy analysis in Studies 2 and 3, 62% were adults and 38% were pediatric patients aged 16 years or younger.

- In Study 2, 50% of patients were female, 70% were White, and the median BMI was 40 kg/m^2(range: 26.6 53.3) at baseline.
- In Study 3, 73% of patients were female, 91% were White, and the median BMI was 46.6 kg/m^2(range: 35.8 64.6) at baseline.

Effect of IMCIVREE on Body Weight in Patients with Obesity due to POMC, PCSK1, or LEPR Deficiency

In Study 2, 80% of patients with obesity due to POMC or PCSK1 deficiency met the primary endpoint, achieving a ≥10% weight loss after 1 year of treatment with IMCIVREE.

In Study 3, 46% of patients with obesity due to LEPR deficiency achieved a ≥10% weight loss after 1 year of treatment with IMCIVREE (Table 10).

Table 10: Body Weight (kg) – Proportion of IMCIVREE-Treated Patients with Obesity due to POMC, PCSK1, or LEPR Deficiency Who Achieved at Least 10% Weight Loss from Baseline at 1 Year in Studies 2 and 3
Parameter | Statistic | Study 2 (POMC or PCSK1) (N=10) | Study 3 (LEPR) (N=11)
Patients Achieving at Least 10% Weight Loss at Year 1 | n (%) | 8 (80%) | 5 (46%)
Patients Achieving at Least 10% Weight Loss at Year 1 | 95% CI^1 | (44.4%, 97.5%) | (16.8%, 76.6%)
Patients Achieving at Least 10% Weight Loss at Year 1 | P-value^2 | <0.0001 | 0.0002
Abbreviations: CI = confidence interval
Note: The analysis set includes patients who received at least 1 dose of study drug and had at least 1 baseline assessment.
^1From the Clopper-Pearson (exact) method
^2Testing the null hypothesis: Proportion =5%

When treatment with IMCIVREE was withdrawn in the 16 patients who had lost at least 5 kg (or 5% of body weight if baseline body weight was <100 kg) during the 10 week open-label period in Studies 2 and 3, these patients gained an average of 5.5 kg in Study 2 and 5.0 kg in Study 3 over 4 weeks. Re initiation of treatment with IMCIVREE resulted in subsequent weight loss (see Figure 1).

Table 11: Percent Change from Baseline in Weight in IMCIVREE-Treated Patients Aged ≥6 Years with Obesity due to POMC, PCSK1, or LEPR Deficiency at 1 Year in Studies 2 and 3 (Full Analysis Set)
Parameter | Statistic | Study 2 (POMC or PCSK1) (N=10) | Study 3 (LEPR) (N=11)
Baseline Body Weight (kg) | Mean (SD) | 118.7 (37.5) | 133.3 (26.0)
Baseline Body Weight (kg) | Median | 115.0 | 132.3
Baseline Body Weight (kg) | Min, Max | 55.9, 186.7 | 89.4, 170.4
1-Year Body Weight (kg) | Mean (SD) | 89.8 (29.4) | 119.2 (27.0)
1-Year Body Weight (kg) | Median | 84.1 | 120.3
1-Year Body Weight (kg) | Min, Max | 54.5, 150.5 | 81.7, 149.9
Percent Change from Baseline to 1 Year (%) | Mean (SD) | -23.1 (12.1) | -9.7 (8.8)
Percent Change from Baseline to 1 Year (%) | Median | -26.7 | -9.8
Percent Change from Baseline to 1 Year (%) | Min, Max | -35.6, -1.2 | -23.3, 0.1
Percent Change from Baseline to 1 Year (%) | LS Mean^1 | -23.12 | -9.65
Percent Change from Baseline to 1 Year (%) | 95% CI^1 | (-31.9, -14.4) | (-16.0, -3.3)
Percent Change from Baseline to 1 Year (%) | P-value^2 | 0.0003 | 0.0074
Abbreviations: CI = confidence interval; SD = standard deviation
Note: This analysis includes patients who received at least 1 dose of study drug, had at least 1 baseline assessment.
^1ANCOVA model containing baseline body weight as a covariate
^2Testing the null hypothesis: mean percent change=0

Figure 1: Mean Percent Change in Body Weight from Baseline in Patients Aged ≥6 Years with Obesity due to POMC, PCSK1, or LEPR Deficiency by Visit (Study 2 [N=9] and Study 3 [N=7])

BL=Baseline (day of first dose)
V2 to V3 = variable dose titration period (2 to 12 weeks)
V3 to V6 = 10-week open-label treatment period
V6 to V8 = 8-week placebo withdrawal period (4 weeks active, 4 weeks placebo)
V8 to V12 = 32-week open-label treatment period
FV = Final visit; time point for primary efficacy analysis
Note: This figure includes patients who had lost at least 5 kg (or 5% of body weight if baseline body weight was <100 kg) during the 10-week open-label period.

Effect of IMCIVREE on Hunger in Patients with Obesity due to POMC, PCSK1, or LEPR Deficiency

In Studies 2 and 3, patients 12 years and older self-reported their daily maximal hunger in a diary, assessed by the Daily Hunger Questionnaire Item 2. Hunger was scored on an 11-point numeric rating scale from 0 (“not hungry at all”) to 10 (“hungriest possible”). Weekly means of daily hunger scores at Baseline and Week 52 are summarized in Table 12.

Table 12: Daily Hunger Scores – Change from Baseline at 1 Year in IMCIVREE-Treated Patients Aged ≥12 Years with Obesity due to POMC, PCSK1, or LEPR Deficiency in Studies 2 and 3 with Available Hunger Data

Parameter | Statistic | Hunger in 24 Hours
Parameter | Statistic | Study 2 (POMC or PCSK1(N=8) | Study 3 (LEPR) (N=8)
Baseline Hunger Score | Median | 7.9 | 7.0
Baseline Hunger Score | Median | 7.0, 9.1 | 5.0, 8.4
1-Year Hunger Score | Min, Max | 5.5 | 4.4
1-Year Hunger Score | Min, Max | 2.5, 8.0 | 2.1, 8.0
Change from Baseline to 1 Year | Median | -2.0 | -3.4
Change from Baseline to 1 Year | Min, Max | -6.5, -0.1 | -4.7, 1.0
Note: This analysis includes patients aged 12 years and older who received at least 1 dose of study drug and had available data. Three patients in Study 2 had missing hunger data at Week 52.
Hunger score was captured in a daily diary and was averaged to calculate a weekly score for analysis. Hunger ranged from 0 to 10 on an 11-point scale where 0 = “not hungry at all” and 10 = “hungriest possible.”

Hunger scores generally worsened during the double-blind, placebo withdrawal period among those patients who had experienced an improvement from baseline, and scores improved when IMCIVREE was reinitiated.

Supportive of IMCIVREE’s effect on weight loss, there were general numeric improvements in blood pressure, lipids, glycemic parameters, and waist circumference. However, because of the limited number of patients studied and the lack of a control group, the treatment effects on these parameters could not be accurately quantified.

14.3 POMC, PCSK1, and LEPR Deficiency and BBS (Pediatric Patients Aged 2 to Less Than 6 Years)

The safety and efficacy of IMCIVREE for weight reduction in pediatric patients aged 2 to less than 6 years with obesity due to POMC, PCSK1, or LEPR deficiency or BBS were assessed in a 52-week clinical trial [Study 4 (NCT04966741)]. Patients with PCSK1 deficiency were eligible but none enrolled. POMC and LEPR deficiency were confirmed by genetic testing demonstrating biallelic variants interpreted as pathogenic, likely pathogenic, or of undetermined significance; BBS was diagnosed clinically with genetic confirmation. Obesity was defined as baseline BMI ≥97th percentile for age and sex and body weight ≥20 kg.

In Study 4, IMCIVREE dose titration occurred over an 8-week period, followed by a 44-week open-label treatment period with IMCIVREE.

Twelve (12) patients were enrolled (3 patients with POMC deficiency, 4 patients with LEPR deficiency, and 5 patients with BBS); 58% were male; 58% were White, 8% were Asian, and 33% had an unknown or not reported race; 8% were Hispanic or Latino ethnicity and 17% had an unknown or not reported ethnicity; and the mean BMI was 29.9 kg/m^2(range: 19-43 kg/m^2) at baseline.

Efficacy analyses were conducted in all 12 patients at the end of treatment.

Effect of IMCIVREE on BMI in Patients Aged 2 to Less Than 6 Years with POMC or LEPR Deficiency or BBS

In Study 4, 8% of patients discontinued study drug.

The mean percent change in BMI after 52 weeks of IMCIVREE treatment was -33.8%, -13.1%, and -9.7% in patients with POMC deficiency, LEPR deficiency, and BBS, respectively (Table 13).

Table 13: Percent Change from Baseline in BMI after 52 Weeks of IMCIVREE Treatment in Patients Aged 2 to Less Than 6 Years with Obesity due to POMC Deficiency, LEPR Deficiency, or BBS (Study 4)
Statistic | POMC (N=3) | LEPR (N=4) | BBS (N=5)
Baseline BMI (kg/m^2)
N | 3 | 4 | 5
Mean (SD) | 27.8 (1.6) | 39.3 (4.8) | 23.7 (3.5)
Median | 28.4 | 41.2 | 23
Min, Max | 26.0, 28.9 | 32.2, 42.5 | 19.3, 29.0
BMI at Week 52 (kg/m^2)
N | 3 | 4 | 5
Mean (SD) | 18.3 (1.2) | 34.0 (5.0)^2 | 21.4 (3.3)
Median | 18 | 32.7 | 22.2
Min, Max | 17.3, 19.7 | 29.5, 41.1 | 17.9, 25.2
Percent Change from Baseline to 52 Weeks (%)
Mean (SE) | -33.8 (4.7) | -13.1 (5.4)^3 | -9.7 (4.0)
Median | -37.6 | -15.1 | -9
Min, Max | -39.3, -24.3 | -22.1, 0 | -21.6, 2.5
95% CI^1 | -54.1, -13.4 | -30.4, 4.2 | -20.7, 1.3
Abbreviations: CI = confidence interval; SD = standard deviation
^1Two-sided 95% CI is calculated with Student’s t-distribution.
^2Using last observation carried forward (LOCF), the mean BMI (SD), median, min, and max at Week 52 are 34.9 (6.8), 32.7 29.5, and 44.9, respectively. Using observed data only, the mean BMI (SD), median, min, and max at Week 52 are 31.6 (1.9), 32.2, 29.5, and 33.1, respectively.
^3Week 52 results are based off baseline observation carried forward (BOCF) for 1 patient lost to follow up after Week 8. Results using last observation carried forward are -10.8 (-34.4, 12.8) and using observed data excluding 1 patient lost to follow up are –17.4 (-37.2, 2.4).

Supportive of IMCIVREE’s effect on weight loss, general numeric improvements in waist circumference were observed.

16 HOW SUPPLIED/STORAGE AND HANDLING

IMCIVREE injection is supplied as:

- 10 mg/mL, clear to slightly opalescent, colorless to slightly yellow solution in a 1-mL multiple-dose vial for single patient use
- Package of 1 multiple-dose vial: NDC 72829-010-01

Store unopened IMCIVREE vials in the refrigerator at 2°C to 8°C (36°F to 46°F) in the original carton. After removal from the refrigerator, vials may be kept at temperatures ranging from refrigerated to room temperature (2°C to 25°C [36°F to 77°F]) for up to 30 days with brief excursions up to 30°C (86°F). After the vial is punctured (opened), discard after 30 days. See Table 14for a summary of storage conditions for IMCIVREE. Store vials in the original carton.

Table 14 Recommended Storage for IMCIVREE Vials

Storage Condition | Unopened Vial | Opened Vial
2°C to 8°C (36°F to 46°F) | Until the expiration date | Up to 30 days, OR Until the expiration date (whichever is earlier)
2°C to 25°C (36°F to 77°F) with excursions permitted up to 30°C (86°F)^1 | Up to 30 days, OR Until the expiration date (whichever is earlier) | Up to 30 days, OR Until the expiration date (whichever is earlier)
>30°C (>86°F) | Discard and do not use | Discard and do not use
^1If necessary, IMCIVREE may be stored at room temperature (≤30°C [≤86°F]) and then returned to refrigerated conditions

17 PATIENT COUNSELING INFORMATION

Advise the patient or caregiver to read the FDA-approved patient labeling (Patient Information and Instructions for Use).

Disturbance in Sexual Arousal

Inform patients that sexual adverse reactions, including spontaneous erection, may occur in patients treated with IMCIVREE. Advise patients to seek emergency medical treatment if an erection lasts longer than 4 hours [see Warnings and Precautions (5.1)].

Depression and Suicidal Ideation

Inform patients or caregivers that IMCIVREE may cause depression or suicidal ideation. Advise patients or caregivers to report any new or worsening symptoms of depression, suicidal thoughts or behaviors, or unusual changes in mood or behavior [see Warnings and Precautions (5.2)].

Hypersensitivity Reactions

Inform patients that serious hypersensitivity reactions have been reported with use of IMCIVREE. Advise patients on the symptoms of hypersensitivity reactions and instruct them to stop taking IMCIVREE and seek medical advice promptly if such symptoms occur [see Warnings and Precautions (5.3)].

Skin Hyperpigmentation, Darkening of Pre-Existing Nevi, and Development of New Melanocytic Nevi

Inform patients or caregivers that skin darkening occurs in the majority of patients treated with IMCIVREE because of its mechanism of action. This change is reversable upon discontinuation of IMCIVREE. Inform patients and caregivers that the development of new melanocytic nevi may occur. Inform patients or caregivers that they should have a full body skin examination before starting and during treatment with IMCIVREE to monitor these changes [see Warnings and Precautions (5.4)].

Pregnancy

Advise patients who may become pregnant to inform their healthcare provider of a known or suspected pregnancy [see Use in Specific Populations (8.1)].

Lactation

Advise patients that treatment with IMCIVREE is not recommended while breastfeeding [see Use in Specific Populations (8.2)].

Administration

Instruct patients and caregivers how to prepare and administer the correct dose of IMCIVREE and assess their ability to inject subcutaneously to ensure the proper administration of IMCIVREE. Instruct patients to use a 1 mL syringe with a 28- or 29-gauge needle appropriate for subcutaneous injection. [see Dosage and Administration (2.6)].

Manufactured for:

Rhythm Pharmaceuticals, Inc.
222 Berkeley Street, Suite 1200
Boston, MA 02116

© 2024, Rhythm Pharmaceuticals, Inc. All rights reserved.
IMCIVREE is a registered trademark of Rhythm Pharmaceuticals, Inc.

PATIENT INFORMATION

IMCIVREE™ [im-SIV-ree]
(setmelanotide)
injection, for subcutaneous use

What is IMCIVREE?

- IMCIVREE is a prescription medicine used in adults and children 2 years of age and older with obesity due to:
  - Bardet-Biedl syndrome (BBS) to help them lose weight and keep the weight off.
  - The genetic conditions proopiomelanocortin (POMC), proprotein convertase subtilisin/kexin type 1 (PCSK1), or leptin receptor (LEPR) deficiency, to help them lose weight and keep the weight off.
- Your healthcare provider should order a genetic test to confirm POMC, PCSK1, or LEPR deficiency before you start using IMCIVREE.
- IMCIVREE is not for use in people with the following conditions because it may not work:
  - Obesity due to suspected POMC, PCSK1, or LEPR deficiency not confirmed by genetic testing or with benign or likely benign genetic testing results.
  - Other types of obesity not related to BBS or POMC, PCSK1, or LEPR deficiency, including obesity associated with other genetic conditions and general obesity.

It is not known if IMCIVREE is safe and effective in children under 2 years of age.

Do not use IMCIVREE if youhave had a serious allergic reaction to setmelanotide or any of the ingredients in IMCIVREE. Serious allergic reactions, including a severe allergic reaction called anaphylaxis, can happen when you use IMCIVREE. See the end of this Patient Information leaflet for a complete list of ingredients in IMCIVREE.

Before using IMCIVREE, tell your healthcare provider about all your medical conditions, including if you:

- have or have had areas of darkened skin, including skin discoloration (hyperpigmentation).
- have or have had depression, or suicidal thoughts or behavior.
- have had a prior allergic reaction to setmelanotide or any of the ingredients in IMCIVREE.
- have kidney problems.
- are pregnant or planning to become pregnant. Losing weight while pregnant may harm your unborn baby. Your healthcare provider may stop your treatment with IMCIVREE if you become pregnant. Tell your healthcare provider if you become pregnant or think you might be pregnant during treatment with IMCIVREE.
- are breastfeeding or plan to breastfeed. It is not known if IMCIVREE passes into your breastmilk. You should not breastfeed during treatment with IMCIVREE.

Tell your healthcare provider about all the medicines you take,including prescription and over-the-counter medicines, vitamins, and herbal supplements.

How should I use IMCIVREE?

- See the detailed Instructions for Useto learn how to prepare and inject IMCIVREE.
- IMCIVREE is given as an injection under your skin (subcutaneous) by you or a caregiver.
- A healthcare provider should show you or your caregiver how to prepare and inject your dose of IMCIVREE before injecting for the first time. Do not try to inject IMCIVREE unless you have been trained by a healthcare provider.
- Use IMCIVREE exactly as prescribed by your healthcare provider.
- IMCIVREE should be injected 1 time each day when you first wake up. IMCIVREE can be given with or without food.
- If you miss a dose of IMCIVREE, inject your next dose at the regularly scheduled time the next day.

What are the possible side effects of IMCIVREE?

IMCIVREE may cause serious side effects, including:

- Male and female sexual function problems.IMCIVREE can cause an erection that happens without any sexual activity in males (spontaneous penile erection) and unwanted sexual reactions (changes in sexual arousal that happen without any sexual activity) in females. If you have an erection lasting longer than 4 hours, get emergency medical help right away.
- Depression and suicidal thoughts or actions.You or a caregiver should call your healthcare provider right away if you have any new or worsening symptoms of depression, suicidal thoughts or behaviors, or any unusual changes in mood or behavior.
- Serious allergic reactions.Stop taking IMCIVREE and get medical help right away if you have any symptoms of a serious allergic reaction including:
  - swelling of your face, lips, tongue or throat
  - problems breathing or swallowing
  - severe rash or itching
  - fainting or feeling dizzy
  - rapid heartbeat
- Increased skin pigmentation, darkening of skin lesions (moles or nevi) you already have, and development of new skin lesions.These changes happen because of how IMCIVREE works in the body and will go away when you stop using IMCIVREE. You should have a full body skin exam before starting and during treatment with IMCIVREE to check for skin changes.
- Benzyl alcohol toxicity.Benzyl alcohol is a preservative in IMCIVREE. Benzyl alcohol can cause serious side effects, including death, in premature and low-birth weight infants, who have received medicines that contain benzyl alcohol. IMCIVREE should not be used in premature and low-birth weight infants.

The most common side effects of IMCIVREE include:

- darkening of the skin
- injection site reactions
- nausea
- headache
- diarrhea
- stomach pain
- vomiting
- depression
- erection that happens without any sexual activity in males

These are not all the possible side effects of IMCIVREE.

Call your doctor for medical advice about side effects. You may report side effects to FDA at 1-800-FDA-1088.
You may also report side effects to Rhythm Pharmaceuticals at 1-833-789-6337.

General information about the safe and effective use of IMCIVREE.

Medicines are sometimes prescribed for purposes other than those listed in a Patient Information leaﬂet. Do not use IMCIVREE for a condition for which it was not prescribed. Do not give IMCIVREE to other people, even if they have the same symptoms that you have. It may harm them. You can ask your pharmacist or healthcare provider for information about IMCIVREE that is written for health professionals.

What are the ingredients in IMCIVREE?

Active ingredient:setmelanotide

Inactive ingredients:benzyl alcohol, carboxymethylcellulose sodium, edetate disodium dihydrate, N-(carbonyl-methoxypolyethylene glycol 2000)-1, 2-distearoyl- glycero-3-phosphoethanolamine sodium salt, mannitol, phenol, hydrochloric acid, sodium hydroxide and water for injection.

INSTRUCTIONS FOR USE
IMCIVREE™ [im-SIV-ree]
(setmelanotide)
injection, for subcutaneous use

This Instructions for Use contains information on how to inject IMCIVREE. Read and follow these instructions before injecting IMCIVREE.

Important Information You Need to Know Before Injecting IMCIVREE

- IMCIVREE is for injection under the skin only (subcutaneous injection). Do notinject IMCIVREE into a vein or muscle.
- The IMCIVREE vial may be used to give more than 1 dose of medicine (multiple-dose vial) but is for single patient use only and should not be shared with other patients.
- Inject IMCIVREE 1 time each day when you first wake up.
- Take IMCIVREE with or without food.
- IMCIVREE is given by you or a caregiver. A healthcare provider will show you or your caregiver how to inject your dose of IMCIVREE before you inject for the first time. Ask your healthcare provider or call IMCIVREE Guidance, Partnership, Support (GPS) at 1-844-YOUR-GPS (1-844-968-7477) if you have questions.

Important note:

- Only use the syringes and needles provided to you for use with IMCIVREE.
- Always use a new syringe and needle for each injection to prevent contamination.
- Throw away used syringes and needles in a puncture-resistant, disposable sharps container as soon as you finish giving the injection. See “Disposing of IMCIVREE”at the end of these instructions.
- Do notreuse or share your needles with other people.
- Do notrecap the needle. Recapping the needle can lead to a needle stick injury.

Understanding Your IMCIVREE Dose

Calculate the number of doses of IMCIVREE in each vial:

- Each unopened IMCIVREE vial contains 10 milligrams (mg) of medicine in 1 milliliter (mL) of solution.
- The vial will contain both medicine and air. Most of the vial will be filled with air.
- Your healthcare provider will determine your dose of medicine in milligrams (mg).
- The IMCIVREE vial may be used to give more than 1 dose of medicine (multiple-dose vial).
- Use Figure Ato see how many times you may use each vial based on your prescribed dose.
- Do notuse more doses from a single vial than listed in Figure A

Preparing to Inject IMCIVREE

Step 1 Gather your supplies.

- Gather the supplies you will need for your injection (Figure B).
- Place your supplies on a clean, flat work surface.

Step 2 Check your IMCIVREE vial.

- Check the expiration (Exp) date on the vial label (Figure C).
- Check the liquid. The liquid should look clear to almost clear and colorless to slightly yellow. The liquid should be free of particles.
- Do notuse if:
  - The expiration (Exp) date has passed.
  - The liquid is cloudy.
  - There are particles floating in the vial.
  - The plastic cap on a new vial is broken or missing.

Step 3 Prepare your IMCIVREE vial.

- Allow the vial to reach room temperature.
  - Remove the vial from the refrigerator 15 minutes before injection.
  - You can also warm the vial by rolling it gently between the palms of your hands for 60 seconds (Figure D).
- Do nottry to warm the vial by using a heat source such as hot water or a microwave.
- Do notshake the vial.
- Wash your hands with soap and warm water.

- If using a new vial, remove the plastic cap (Figure E) and throw away this plastic cap in the trash. Do not put the plastic cap back on the vial.

- Clean the top of the vial rubber stopper with 1 alcohol wipe (Figure F). Throw away the alcohol wipe in the trash.
- Do notremove the vial rubber stopper.

Step 4 Prepare the syringe.

When measuring your dose, be sure to read the markings starting from the end closest to the black rubber stopper (Figure G).

- Fill the syringe with air.
  - Keep the protective needle cap on the syringe.
  - Pull back on the plunger until the end of the black rubber stopper stops at your dose. Fill the syringe with air equal to the amount of the medicine to be given (Figure H).
- Remove the protective needle cap from the syringe.
  - Remove the protective needle cap by pulling it straight off and away from your body.

- Insert the needle.
  - Place the vial on the clean, flat work surface.
  - With the vial in the upright position, place the syringe directly over the vial and insert the needle straight down into the center of the vial rubber stopper (Figure I).
  - Push the air from the syringe into the vial.

- Fill the syringe with IMCIVREE
  - Keep the needle in the vial and slowly turn the vial upside down.
  - Make sure to keep the tip of the needle in the medicine (Figure J).
- Slowly pull back on the plunger to fill the syringe with the amount of IMCIVREE needed for your prescribed dose.
- Be careful not to pull the plunger out of the syringe.
- Do notuse more than 1 vial of IMCIVREE to give a single dose. Use a new vial that has enough medicine for your prescribed dose.

- Check for large air bubbles (Figure K).
  - Keep the needle in the vial and check the syringe for large air bubbles.

What to do if you see large air bubbles:

Large air bubbles can reduce the dose of medicine you receive. To remove large air bubbles:

- Gently tap the side of the syringe with your finger to move the air bubbles to the top of the syringe.
- Move the tip of the needle above the medicine and slowlypush the plunger up to push the large air bubbles back into the vial.
- After the large air bubbles are removed, pull back on the plunger again (more slowly this time) to fill the syringe with your prescribed dose of medicine.

- Withdraw the needle
  - Return the vial to an upright position and place it on the clean, flat work surface.
  - While holding the vial with 1 hand and the barrel of the syringe between the fingertips of your other hand, pull the needle straight out of the vial (Figure L).
  - Set the syringe down on the clean, flat work surface.
- Make sure the needle does not touch the surface.
- Do notrecap the needle

Injecting IMCIVREE

Step 5 Prepare your injection site.

- Choose the area where you will give the injection. Choose from the following recommended injection sites:
  - belly (abdomen) (Figure M)
  - front of the middle thighs (Figure N)
  - ◦ back of the upper arm (Figure O)
- Be sure to choose an area on the belly (abdomen) at least 2 inches from the belly button.
- Do notinject into the belly button, ribs, and hip bones, as well as scars or moles.
- Do notinject in an area that is red, swollen, or irritated

- Clean the injection site with the second alcohol wipe using a circular motion.
- Do nottouch, fan, or blow on the cleaned area.
- Allow the skin to dry for about 10 seconds.

Rotate your injection site each day.

You should use a different injection site each time you give an injection, at least 1 inch away from the area you used for your previous injection. You may want to use a calendar or diary to record your injection sites.

Step 6 Place your hands for the injection.

- With 1 hand, pinch about 2 inches of skin at the injection site between your thumb and index (pointer) finger (Figure P). Pinching the skin is important to help make sure that you inject the medicine under the skin (into fatty tissue) but not any deeper (into the muscle).

Step 7 Inject and release.

- With your other hand, place the syringe between the thumb and index (pointer) finger.
- Hold the middle of the syringe (where the markings are printed) at a 90-degree angle to your body and push the needle straight into the injection site (Figure Q). Make sure that you push the needle all the way into the skin.
- Do nothold or push on the plunger while inserting the needle.

- Slowly push the plunger down to inject the medicine (Figure R)
- Keep the needle in your skin and count to 5 to make sure that all the medicine is given.
- Let go of the pinched skin and remove the needle.
- Use the gauze pad to gently apply pressure to the injection site.
- Do notrecap the needle.

Tips for giving injections to children

When giving a child an injection, it can help to have the child do other things. Have the child:

- squeeze something soft like a ball or stuffed animal.
- slowly breathe in and out.
- sing a song, count, or name favorite colors or animals.

Storing IMCIVREE

- Store unopened and opened vials in the original carton to protect them from light.
- Store opened vials of IMCIVREE in the refrigerator between 36°F to 46°F (2°C to 8°C). If needed, opened vials may be removed from the refrigerator and stored at temperatures ranging from refrigerated to room temperature (36°F to 77°F (2°C to 25°C)). Vials may be returned to the refrigerator. Throw away all opened vials 30 days after first opening, even if some medicine is still left in the vial.
- Unopened vials of IMCIVREE may be stored in the refrigerator between 36°F to 46°F (2°C to 8°C) until the expiration date. If needed, unopened vials may also be removed from the refrigerator and stored at temperatures ranging from refrigerated to room temperature (36°F to 77°F (2°C to 25°C)) for up to 30 days. Vials may be returned to the refrigerator. Throw away IMCIVREE if it has been more than 30 days since the vial was first removed from the refrigerator.
- If necessary, vials may be stored at room temperature below 86°F (30°C) and may be returned to refrigerated conditions. Throw away IMCIVREE that has been stored above 86°F (30°C).
- Write the date on the carton when you first open the vial.
- Keep IMCIVREE, needles, syringes, and all medicines out of the reach of children.

Disposing of IMCIVREE

- Alcohol wipes, used gauze pads, and vials can be thrown away in the trash. Throw away (dispose of) used syringes and needles in a puncture-resistant container, such as an FDA-cleared sharps disposal container immediately after use (Figure S).
  Do notthrow away (dispose of) syringes and needles in your household trash.
  If you do not have an FDA-cleared sharps disposal container, you may use a household container that is:
  - made of a heavy-duty plastic,
  - can be closed with a tight-fitting, puncture-resistant lid, without sharps being able to come out,
  - upright and stable during use,
  - leak-resistant, and
  - properly labeled to warn of hazardous waste inside the container.
  When your sharps disposal container is almost full, you will need to follow your community guidelines for the right way to dispose of your sharps disposal container. There may be state or local laws about how you should throw away used syringes and needles. For more information about safe sharps disposal and for specific information about sharps disposal in the state that you live in, go to the FDA’s website at: http://www.fda.gov/safesharpsdisposal.
- Do not dispose of your used sharps disposal container in your household trash unless your community guidelines permit this.
- Do not recycle your used sharps disposal container.
  Note: Keep your sharps disposal container out of the reach of children and pets.

For more information about IMCIVREE, including how to inject IMCIVREE, go to www.IMCIVREE.comor call 1-844-YOUR-GPS (1-844-968-7477).

IMCIVREE is Manufactured for:
Rhythm Pharmaceuticals, Inc
222 Berkeley Street, Suite 1200
Boston, MA 02116

Made in France

IMCIVREE is a trademark of Rhythm Pharmaceuticals, Inc.
©2020 Rhythm Pharmaceuticals, Inc.

This Patient Information and Instructions for Use have been approved by the U.S. Food and Drug Administration.
Revised [June 2025]